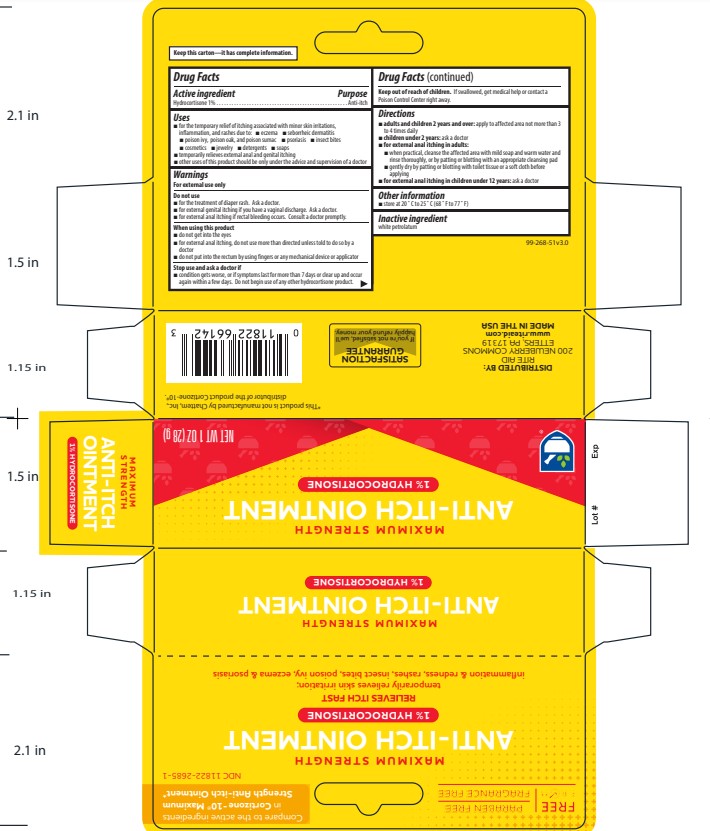 DRUG LABEL: Rite Aid Hydrocortisone
NDC: 11822-2685 | Form: OINTMENT
Manufacturer: Rite Aid
Category: otc | Type: HUMAN OTC DRUG LABEL
Date: 20231212

ACTIVE INGREDIENTS: HYDROCORTISONE 1 g/100 g
INACTIVE INGREDIENTS: WHITE PETROLATUM

Rite Aid Hydrocortisone Ointment

Active ingredient

Hydrocortisone 1%

Purpose

Anti-itch

Uses

For the temporary relief of itching associated with minor skin irritations, inflammation, and rashes due to:

- eczema
- seborrheic dermatitis
- poison ivy, poison oak, and poison sumac
- psoriasis
- insect bites
- cosmetics
- jewelry
- detergents
- soaps

temporarily relieves external anal and genital itching

other uses of this product should be only under the advise and supervision of a doctor

Warnings

For external use only

Do not use

- for the treatment of diaper rash. Ask a doctor.
- for external genital itching if you have a vaginal discharge. Ask a doctor.
- for external anal itching if rectal bleeding occurs. Consult a doctor promptly.

When using this product

- do not get in the eyes
- for external anal itching, do not use more than directed unless told to do so by a doctor
- do not put into the rectum by using fingers or any mechanical device or applicator

Stop use and ask a doctor if

- condition gets worse, or if symptoms last for more than 7 days or clear up and occur again within a few days. Do not begin use of any other hydrocortisone product.

Keep out of reach of children.

If swallowed, get medical help or contact a Poison Control Center right away.

Directions

adults and children 2 years and over: apply to affected area not more than 3 to 4 times daily

children under 2 years: ask a doctor

for external anal itching in adults:

- when practical, cleanse the affected area with mild soap and warm water and rinse thoroughly, or by patting or blotting with an appropriate cleansing pad
- gently dry by patting or blotting with toilet tissue or a soft cloth before applying

for external anal itching in children under 12 years: ask a doctor

Other information

- store at 20ºC to 25ºC (68ºF to 77ºF)

Inactive ingredient

white petrolatum